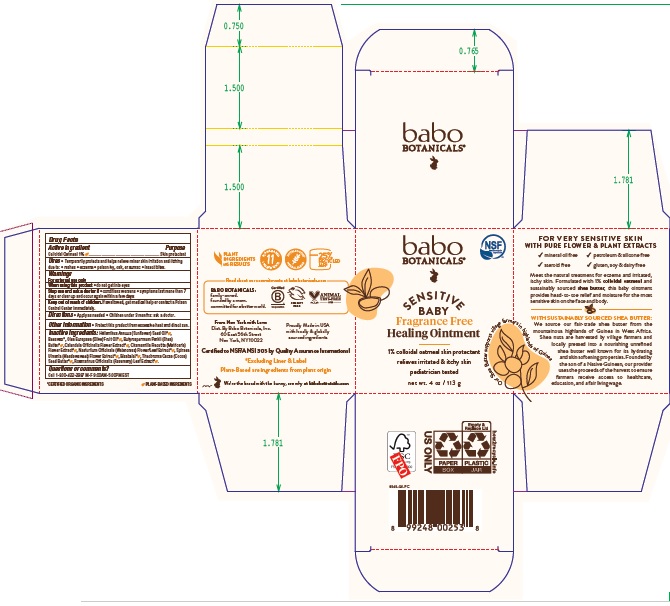 DRUG LABEL: Babo Botanicals Sensitive Baby Healing
NDC: 79265-8655 | Form: OINTMENT
Manufacturer: Babo Botanicals, Inc.
Category: otc | Type: HUMAN OTC DRUG LABEL
Date: 20231023

ACTIVE INGREDIENTS: OATMEAL 10 mg/1 g
INACTIVE INGREDIENTS: OLIVE OIL; NASTURTIUM OFFICINALE FLOWERING TOP; FILIPENDULA ULMARIA FLOWER; COCOA BUTTER; SHEA BUTTER; CHAMOMILE; CALENDULA OFFICINALIS FLOWER; SUNFLOWER OIL; ROSEMARY; YELLOW WAX; LEVOMENOL

Babo Botanicals Sensitive Baby Healing Ointment

Active Ingredient

Colloidal Oatmeal 1%

Purpose

Skin Protectant

Uses

- Temporarily protects and helps relieve minor skin irritation and itching due to
- rashes
- eczema
- poison ivy ,oak, or sumac
- insect bites

Warnings

For external use only.

When using this product

- do not get into eyes

Stop use and ask a doctor if

- conditions worsens
- symptoms last more than 7 days or clear up and occur again within a few days

Keep out of reach of children

If swallowed, get medical help or contact a Poison Control Center immediately.

Directions

- Apply as needed.
- Children under 3 months: ask a doctor.

Other information

- Protect this product from excessive heat and direct sun.

Inactive Ingredients

Helianthus Annuus (Sunflower) Seed Oil*, Beeswax*, Olea Europoaea (Olive) Fruit Oil*, Butyrospermum Parkii (Shea) Butter*, Calendula Officinalis Flower Extract*, Chamomilla Recutita (Matricaria) Flower Extract*, Nasturtium Officinale (Watercress) Flower/Leaf Extract*, Spiraea Ulmaria (Meadowsweet) Flower Extract*, Bisabolol*, Theobroma Cacao (Cocoa) Seed Butter*, Rosmarinus Officinalis (Rosemary) Leaf Extract*.

*Certified Organic Ingredients

Questions or comments?

Call 1-800-422-2987 M-F 9:00AM-5:00PM EST

Company Information

Dist: by Babo Botanicals, Inc.

60 East 56th Street

New York, NY 10022